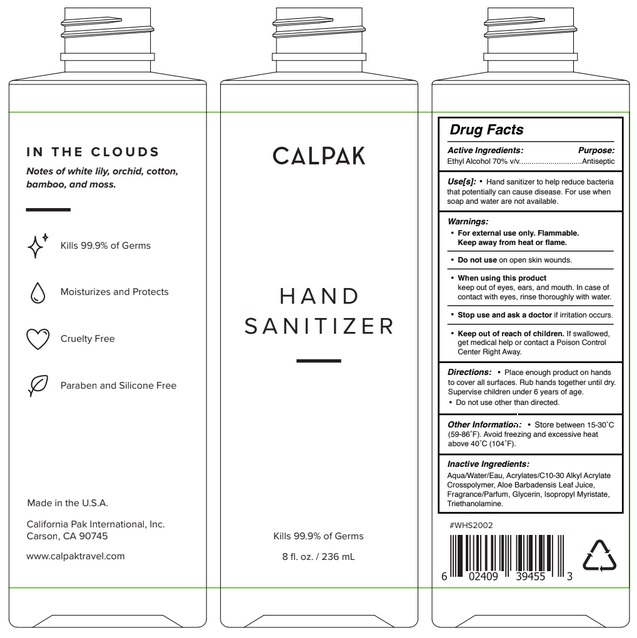 DRUG LABEL: CALPAK
NDC: 80543-001 | Form: GEL
Manufacturer: CALIFORNIA PAK INTERNATIONAL, INC
Category: otc | Type: HUMAN OTC DRUG LABEL
Date: 20200930

ACTIVE INGREDIENTS: ALCOHOL 70 mL/100 mL
INACTIVE INGREDIENTS: WATER; CARBOMER INTERPOLYMER TYPE A (ALLYL SUCROSE CROSSLINKED); ALOE VERA LEAF; GLYCERIN; ISOPROPYL MYRISTATE; TROLAMINE

Active Ingredient

Ethyl Alcohol 70% v/v.

Purpose

Antiseptic

Use

Hand Sanitizer to help reduce bacteria that potentially can cause disease. For use when soap and water are not available.

Warnings

For external use only. Flammable. Keep away from heat or flame

Do not use on open skin wounds.

When using this product keep out of eyes, ears, and mouth. In case of contact with eyes, rinse eyes thoroughly with water.
Stop use and ask a doctor if irritation occurs.

Keep out of reach of children. If swallowed, get medical help or contact a Poison Control Center right away.

Directions

- Place enough product on hands to cover all surfaces. Rub hands together until dry.
- Supervise children under 6 years of age.
- Do not use other than directed.

Other information

- Store between 15-30°C (59-86°F)
- Avoid freezing and excessive heat above 40°C (104°F)

Inactive ingredients

Aqua/Water/Eau, Acrylates/C10-30 Alkyl Acrylate Crosspolymer, Aloe Barbadensis Leaf Juice, Fragrance/Parfum, Glycerin, Isopropyl Myristate, Triethanolamine.